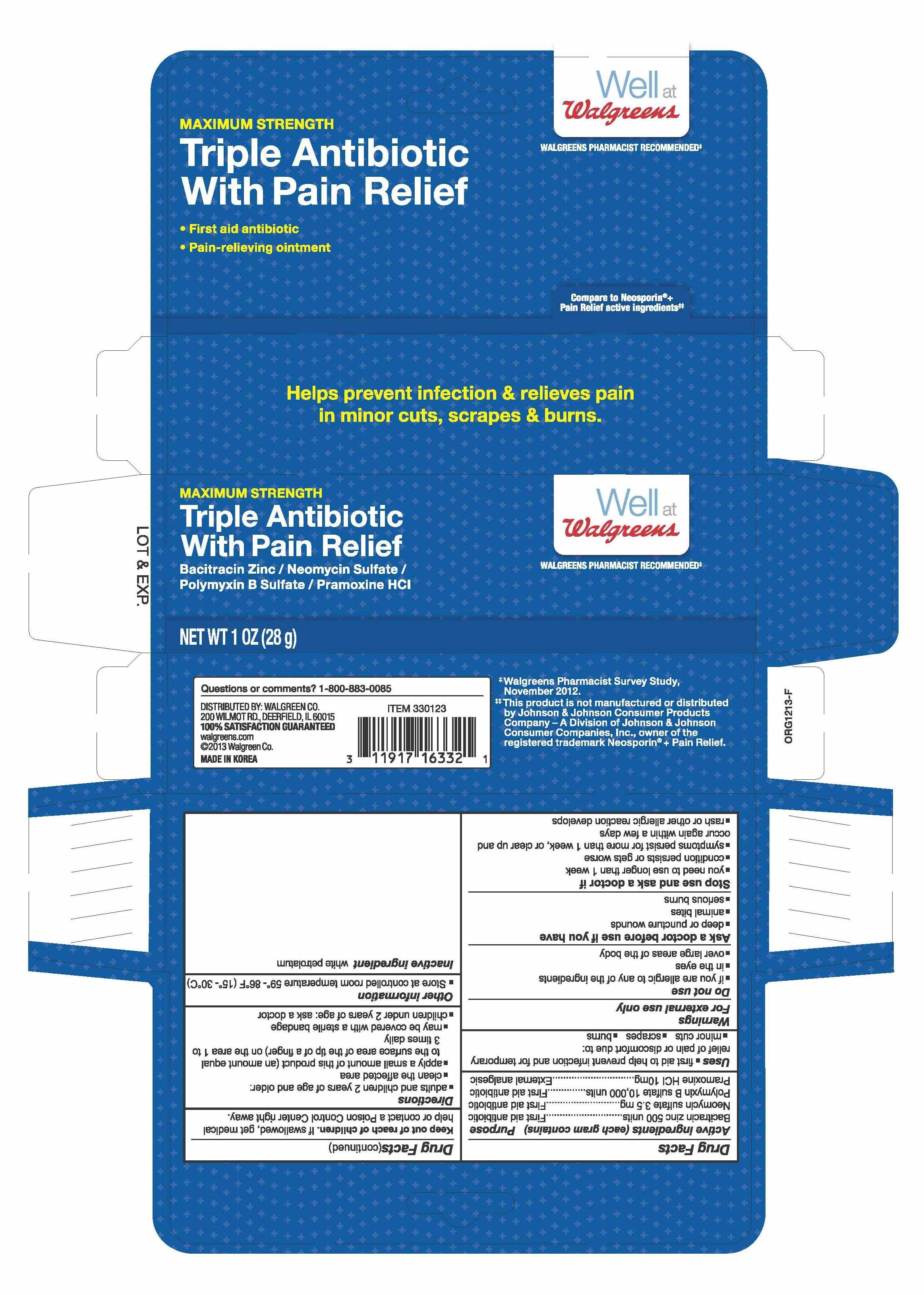 DRUG LABEL: Triple Antibiotic with Pain Relief
NDC: 0363-0123 | Form: OINTMENT
Manufacturer: Walgreen Company
Category: otc | Type: HUMAN OTC DRUG LABEL
Date: 20140327

ACTIVE INGREDIENTS: BACITRACIN ZINC 500 [USP'U]/1 g; NEOMYCIN SULFATE 3.5 mg/1 g; POLYMYXIN B SULFATE 10000 [USP'U]/1 g; PRAMOXINE HYDROCHLORIDE 10 mg/1 g
INACTIVE INGREDIENTS: PETROLATUM

MAXIMUM STRENGTH
Triple Antibiotic with Pain Relief
Bacitracin Zinc /Neomycin Sulfate / Polymyxin B Sulfate /Pramoxine HCI

Drug Facts

Active ingredients (in each gram)

Bacitracin zinc, USP 500 units
Neomycin sulfate, USP 3.5 mg
Polymyxin B sulfate, USP 10,000 units
Pramoxine hydrochloride, USP 10 mg

Purposes

First aid antibiotic/Pain reliever

Uses

First aid to help prevent infection and for temporary relief of pain or discomfort due to

- minor cuts
- scrapes
- burns

Warnings

For external use only

Do not use

- in the eyes
- over large areas of the body

Ask a doctor before use if you have

- deep or puncture wounds
- animal bites
- serious burns

Stop use and ask a doctor if

- condition persists or gets worse
- symptoms last for more than 7 days or clear up and come back within a few days
- a rash or other allergic reaction develops

Keep out of reach of children. If swallowed, get medical help or contact a Poison Control Center right away.

Directions

Adults and children 2 years of age and older:

- clean affected area
- apply a small amount of this product (an amount equal to the surface area of the tip of a finger) on the area 1 to 3 times daily
- may be covered with a sterile bandage

Children under 2 years of age: ask a doctor

Other information

- Store at 59° - 86°F (15° - 30°C).
- Before using any medication, read all label directions. Keep carton, it contains important information.

Inactive ingredient

white petrolatum

PRINCIPAL DISPLAY PANEL

Well at Walgreens
WALGREENS PHARMACIST RECOMMENDED
MAXIMUM STRENGTH
Triple Antibiotic with Pain Relief
Bacitracin Zinc /Neomycin Sulfate / Polymyxin B Sulfate /Pramoxine HCI

- First aid antibiotic
- Pain relieving ointment

Compare to Neosporin® +
Pain Relief active ingredients
Helps prevent infection & relieves pain in minor cuts, scrapes & burns

NET WT 0.5 OZ (14 g)